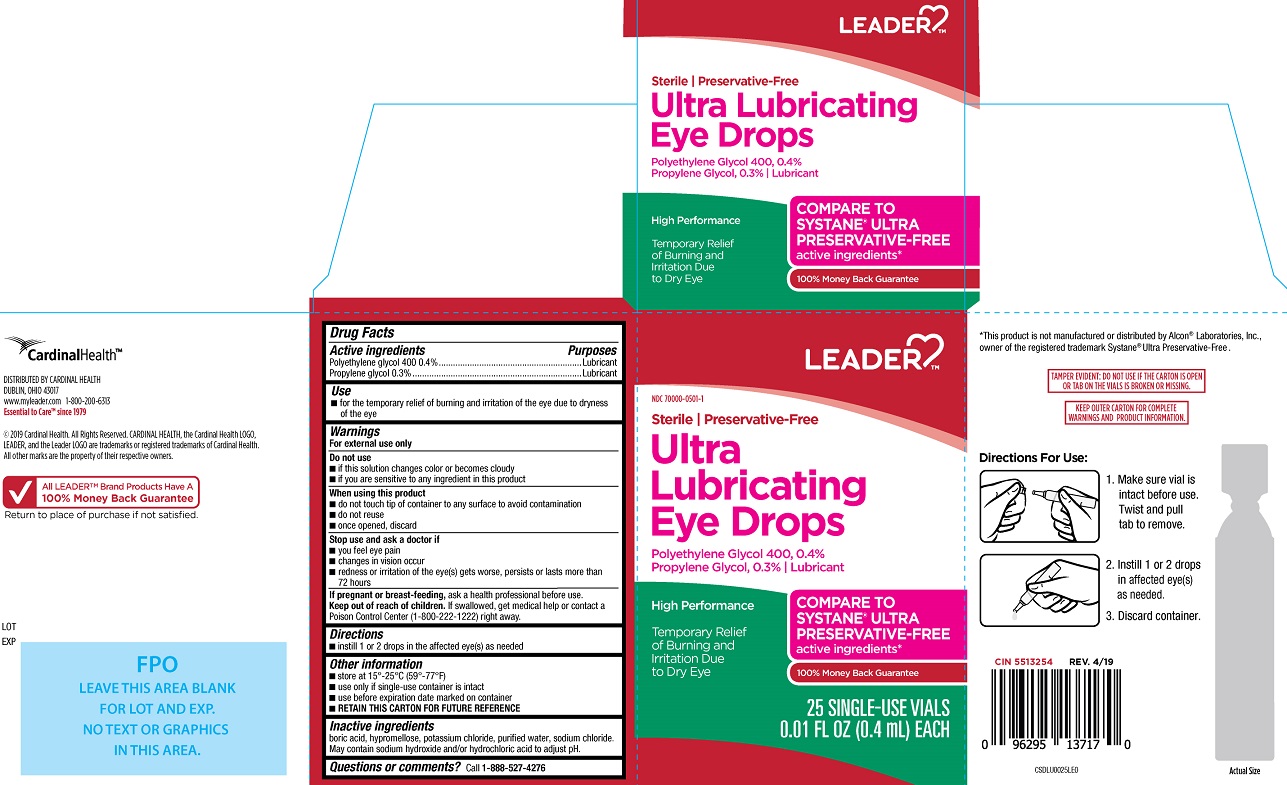 DRUG LABEL: Leader Preservative-Free Ultra Lubricating Eye Drops
NDC: 70000-0501 | Form: SOLUTION/ DROPS
Manufacturer: Cardinal Health
Category: otc | Type: HUMAN OTC DRUG LABEL
Date: 20240907

ACTIVE INGREDIENTS: POLYETHYLENE GLYCOL 400 0.4 g/100 mL; PROPYLENE GLYCOL 0.3 g/100 mL
INACTIVE INGREDIENTS: BORIC ACID; HYPROMELLOSES; POTASSIUM CHLORIDE; WATER; SODIUM CHLORIDE; SODIUM HYDROXIDE; HYDROCHLORIC ACID

Leader Preservative-Free Ultra Lubricating Eye Drops (PLD)

Active ingredients

Polyethylene glycol 400 0.4%
Propylene glycol 0.3%

Purpose

Polyethylene glycol 400............. Lubricant
Propylene glycol............ Lubricant

Uses
• for the temporary relief of burning and irritation of the eye due to dryness of the eye

Warnings
For external use only

Do not use
• if this product changes color or becomes cloudy
• if you are sensitive to any ingredient in this product

When using this product
• do not touch the tip of container to any surface to avoid contamination
• do not reuse

- once opened, discard

Stop use and ask a doctor if
• you feel eye pain
• changes in vision occur
• redness or irritation of the eye(s) gets worse, persists or lasts more than 72 hours

PREGNANCY

If pregnant or breast-feeding, ask a health professional before use.

Keep out of reach of children
If swallowed, get medical help or contact a Poison Control Center (1-800-222-1222) right away.

Directions
• Instill 1 or 2 drops in the affected eye(s) as needed

Other information

- store at 15°-25°C (59°-77°F)
- use only if single-use container is intact
- use before expiration date marked on container
- RETAIN THIS CARTON FOR FUTURE REFERENCE

Inactive ingredients

boric acid, hypromellose, potassium chloride, purified water, sodium chloride. May contain sodium hydroxide and/or hydrochloric acid to adjust pH.

Questions or comments? Call 1-888-527-4276